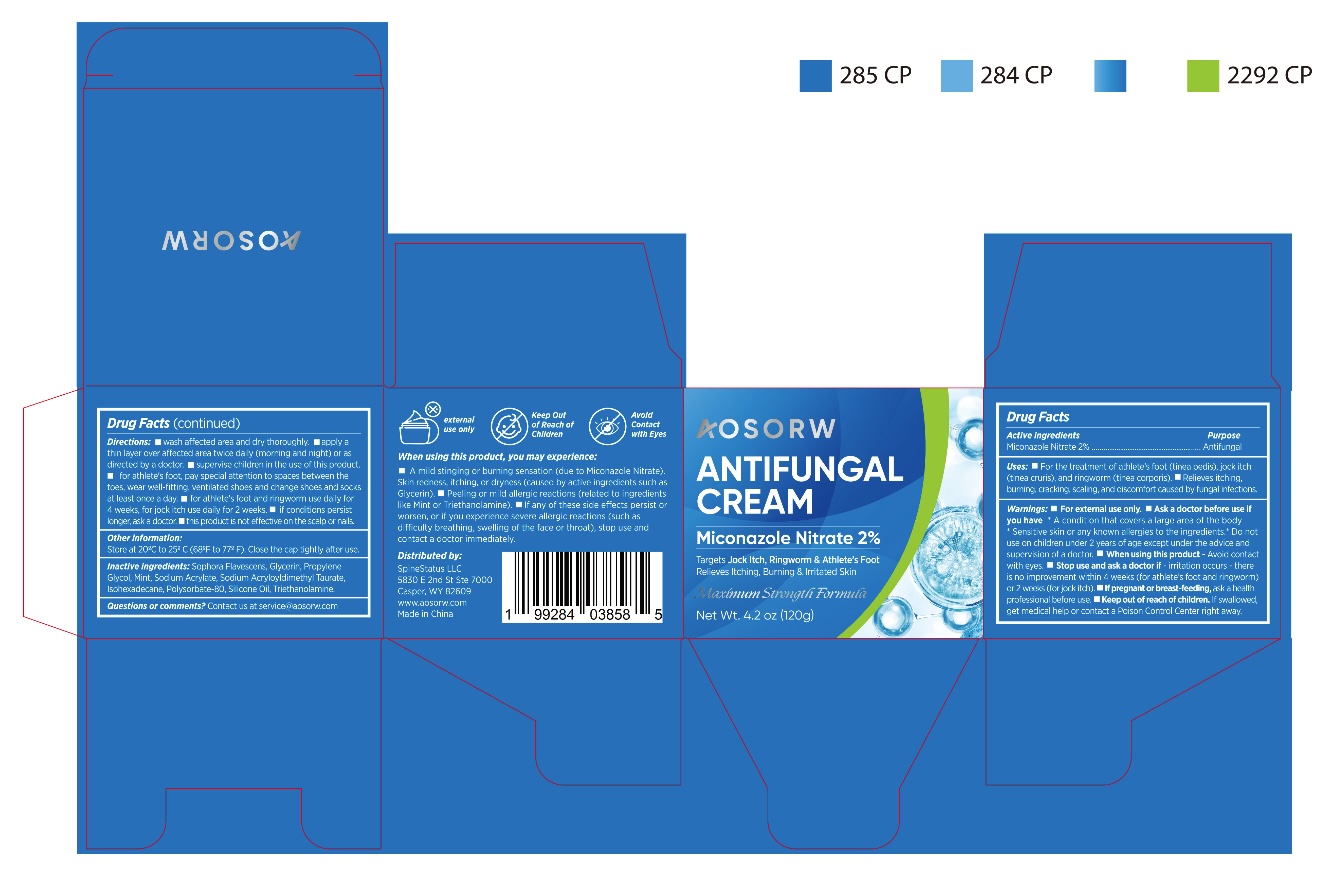 DRUG LABEL: Aosorw Antifungal Cream
NDC: 85498-011 | Form: CREAM
Manufacturer: SpineStatus LLC
Category: otc | Type: HUMAN OTC DRUG LABEL
Date: 20251103

ACTIVE INGREDIENTS: MICONAZOLE NITRATE 2 g/100 g
INACTIVE INGREDIENTS: GLYCERIN; SODIUM ACRYLOYLDIMETHYLTAURATE; DIMETHICONE; PROPYLENE GLYCOL; ISOHEXADECANE; PEPPERMINT OIL; SODIUM ACRYLATE; POLYSORBATE 80; SOPHORA FLAVESCENS ROOT; TRIETHANOLAMINE

Initial Drug Listing - AOSORW ANTIFUNGAL CREAM

ACTIVE INGREDIENT

Miconazole Nitrate 2%

PURPOSE

Antifungal

INDICATIONS AND USAGE

- For the treatment of athlete's foot (tinea pedis), jock itch (tinea cruris), ringworm (tinea corporis).
- Relieves itching, burning, cracking, scaling, and discomfort caused by fungal infections.

WARNINGS

For external use only

ASK DOCTOR

before use if you have

- a condition that covers a large area of the body
- sensitive skin or any known allergies to the ingredients

DO NOT USE

on children under 2 years of age except under the advice and supervision of a doctor.

WHEN USING

avoid contact with eyes.

STOP USE

and ask a doctor if

- irritation occurs.
- there is no improvement within 4 weeks (for athlete's foot and ringworm) or 2 weeks (for jock itch).

PREGNANCY OR BREAST FEEDING

ask a health professional before use

KEEP OUT OF REACH OF CHILDREN

If swallowed, get medical help or contact a Poison Control Center right away.

DOSAGE AND ADMINISTRATION

- wash affected area and dry thoroughly.
- apply a thin layer over affected area twice daily (morning and night) or as directed by a doctor.
- supervise children in the use of this product.
- for athlete's foot and ringworm use daily for 4 weeks, for jock itch use daily for 2 weeks.
- if conditions persist longer, ask a doctor.
- this product is not effective on the scalp or nails.

OTHER SAFETY INFORMATION

Store at 20ºC to 25ºC (68ºF to 77ºF).
Close the cap tightly after use.

INACTIVE INGREDIENT

Sophora Flavescens Root, Glycerin, Propylene Glycol, Peppermint Oil, Sodium Acrylate, Sodium Acryloyldimethyl Taurate, Isohexadecane, Polysorbate-80, Dimethicone, Triethanolamine

QUESTIONS

Contact us at service@aosorw.com